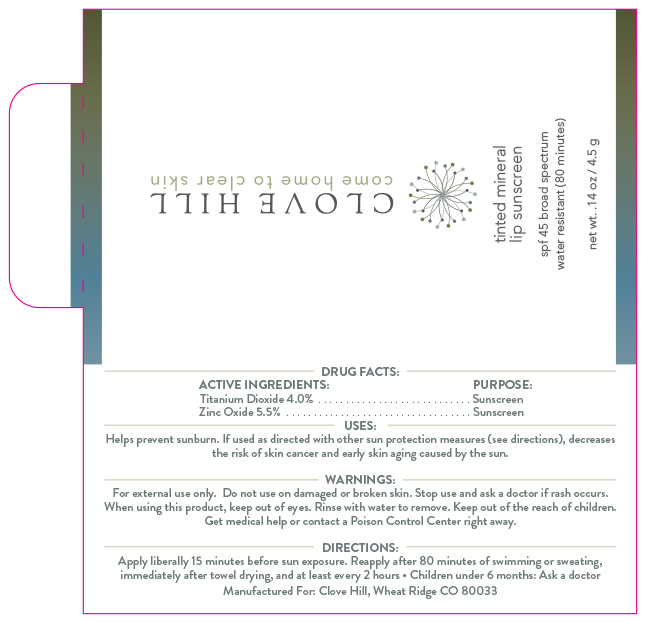 DRUG LABEL: Tinted Mineral Lip Sunscreen
NDC: 82746-212 | Form: STICK
Manufacturer: Clove Hill LLC
Category: otc | Type: HUMAN OTC DRUG LABEL
Date: 20251030

ACTIVE INGREDIENTS: TITANIUM DIOXIDE 40 mg/1 g; ZINC OXIDE 55 mg/1 g
INACTIVE INGREDIENTS: CETEARYL ISONONANOATE; POLYGLYCERYL-3 DIISOSTEARATE; ALPHA-TOCOPHEROL ACETATE; ASCORBIC ACID; CITRIC ACID; ETHYLHEXYL PALMITATE; C12-15 ALKYL BENZOATE; HELIANTHUS ANNUUS (SUNFLOWER) SEED WAX; PEG-8; CI 77499; ALUMINUM HYDROXIDE; ZINGIBER OFFICINALE (GINGER) ROOT OIL; PEG/PPG-15/15 DIMETHICONE; DIPROPYLENE GLYCOL CAPRATE/CAPRYLATE DIESTER; ALUMINUM STEARATE; LECITHIN, SOYBEAN; CERESIN; CETYL DIMETHYLBUTYL ETHER; HEXYLDECYL LAURATE; ASCORBYL PALMITATE; CI 77491; ALUMINA; CI 77492; HEXYLDECANOL; TOCOPHEROL; STEARIC ACID; POLYHYDROXYSTEARIC ACID (2300 MW)

ACTIVE INGREDIENT

Titanium Dioxide: 4% Zinc Oxide: 5.5%

PURPOSE

Sunscreen

INDICATIONS AND USAGE

Helps Prevent Sunburn. If used as directed with other sun protection measures (see “Directions”), decreases the risk of skin cancer and early skin aging caused by the sun.

WARNINGS

For external use only. Do not use on broken or damaged skin. Stop use and ask a doctor if rash occurs. When using this product, keep out of eyes. Rinse with water to remove. Keep out of reach of children. If swallowed, get medical help or contact a poison control center right away.

Keep out of reach of children

DOSAGE AND ADMINISTRATION

Apply liberally 15 minutes before sun exposure. Use a water-resistant product if swimming or sweating. Reapply at least every 2 hours. Children under 6 months: Ask a doctor. Sun Protection Measures: Spending time in the sun increases your risk of skin cancer and early skin aging. To decrease this risk, regularly use a sunscreen with a Broad-Spectrum SPF value of 15 or higher and other sun protection measures including: Limit time in the sun, especially from 10 a.m. - 2 p.m. Wear long-sleeved shirts, pants, hats and sunglasses

INACTIVE INGREDIENT

Alumina, Aluminum Hydroxide, Aluminum Stearate, Asorbic Acid, Ascorbyl Palmitate, C12-15Alkyl Benzoate, Cetearyl Isononanoate, Cetyl PEG/PPG-15/15 Butyl Ether Dimethicone, Citric Acid, Dipropylene Glycol Dicaprylate-Caprate, Ethylhexyl Palmitate, Flavor, Helianthus annuus (Sunflower) Seed Wax, Hexyldecanol, Hexyldecyl Laurate, Iron Oxide, Lecithin, Ozokerite, PEG-8, Polyglyceryl-3 Diisostearate, Polyhydroxystearic Acid, Stearic Acid, Tocopherol, Tocopheryl Acetate, Zingiber Officinale (Ginger) Root Oil